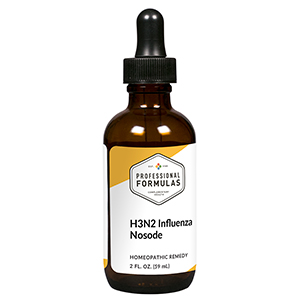 DRUG LABEL: H3N2 Influenza Nosode
NDC: 63083-4449 | Form: LIQUID
Manufacturer: Professional Complementary Health Formulas
Category: homeopathic | Type: HUMAN OTC DRUG LABEL
Date: 20190815

ACTIVE INGREDIENTS: INFLUENZA A VIRUS A/SOUTH AUSTRALIA/55/2014 IVR-175 (H3N2) NEURAMINIDASE ANTIGEN (PROPIOLACTONE INACTIVATED) 12 [hp_X]/59 mL
INACTIVE INGREDIENTS: ALCOHOL; WATER

N49

ACTIVE INGREDIENTS

H3N2 Influenza virus 12X, 30X, 60X, 100X

QUESTIONS

Professional Formulas

PO Box 2034 Lake Oswego, OR 97035

INDICATIONS

For the temporary relief of chills, cough, minor sore throat, occasional headache, muscle aches, or fatigue.*

PURPOSE

*Claims based on traditional homeopathic practice, not accepted medical evidence. Not FDA evaluated.

WARNINGS

Persistent symptoms may be a sign of a serious condition. If symptoms persist or are accompanied by a fever, rash, or persistent headache, consult a doctor. Keep out of the reach of children. In case of overdose, get medical help or contact a poison control center right away. If pregnant or breastfeeding, ask a healthcare professional before use.

Keep out of the reach of children.

PREGNANCY OR BREAST FEEDING

If pregnant or breastfeeding, ask a healthcare professional before use.

DIRECTIONS

Place drops under tongue 30 minutes before/after meals. Adults and children 12 years and over: Take 10 to 15 drops once weekly or monthly. If mild symptoms are present, take 10 drops up to 3 times per day. Consult a physician for use in children under 12 years of age.

OTHER INFORMATION

Tamper resistant. If seal is broken, do not use. After opening, close container tightly and store at room temperature away from heat.

INACTIVE INGREDIENTS

20% ethanol, purified water.

LABEL

Est 1985

Professional Formulas

Complementary Health

H3N2 Influenza Nosode

Homeopathic Remedy

2 FL. OZ. (59 mL)